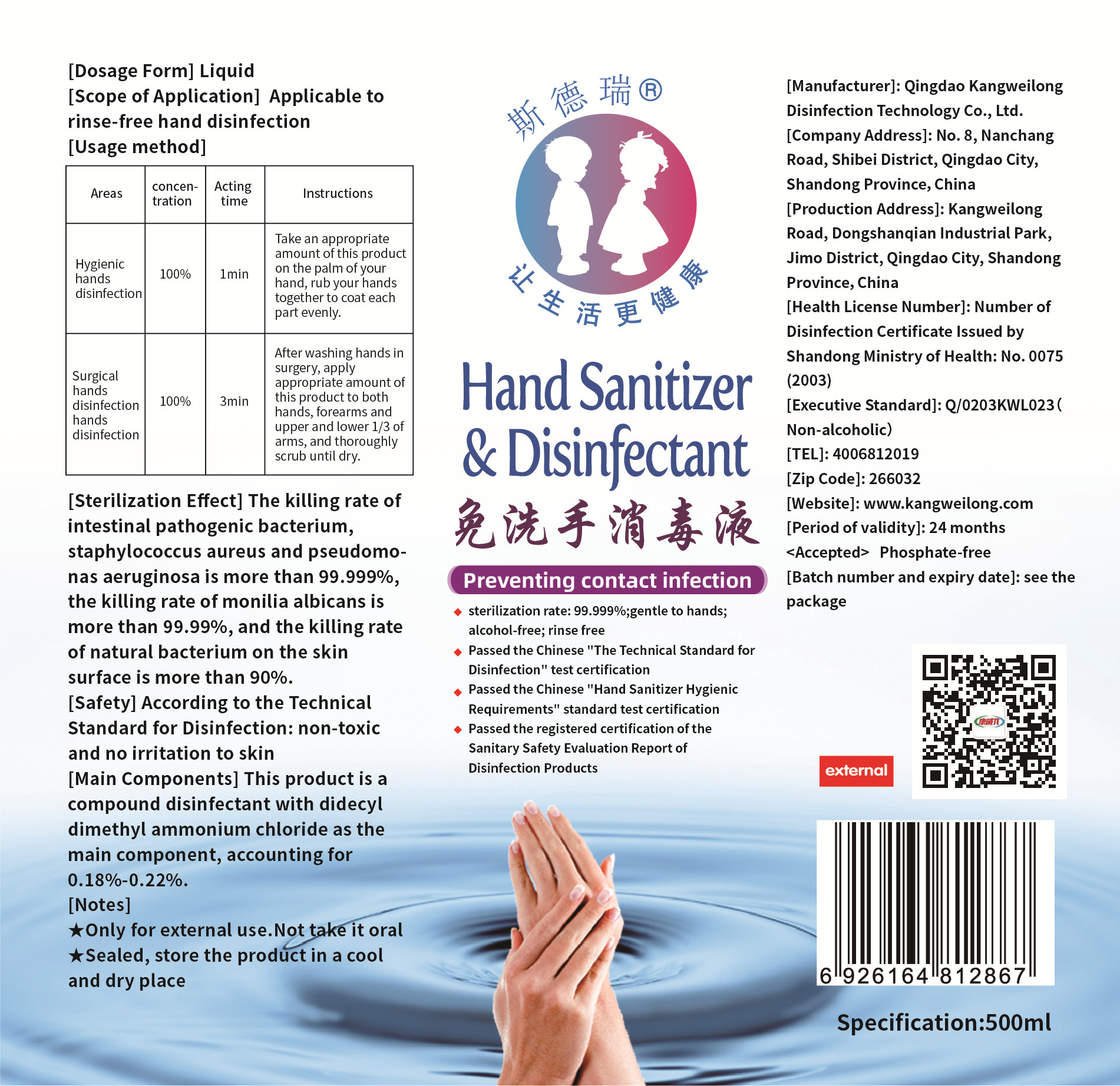 DRUG LABEL: Steri Hand sanitizer without washing
NDC: 54529-002 | Form: LIQUID
Manufacturer: Qingdao Kangweilong Disinfection Technology Co.,Ltd.
Category: otc | Type: HUMAN OTC DRUG LABEL
Date: 20200427

ACTIVE INGREDIENTS: DIDECYLDIMONIUM CHLORIDE 1 mg/500 mL
INACTIVE INGREDIENTS: WATER; CETRIMONIUM CHLORIDE

DOSAGE AND ADMINISTRATION

Sealed, store the product in a cool and dry place.

INACTIVE INGREDIENT

Pure water

Cetyl trimethyl ammonium chloride

INDICATIONS AND USAGE

Hygienic hands disinfection:Take an appropriate amount of this product on the palm of your hand, rub your hands together to coat each
part evenly.need 1 min.

Surgical hands disinfection hands disinfection:After washing hands in surgery, apply appropriate amount of this product to both hands, forearms and upper and lower 1/3 of arms, and thoroughly scrub until dry.need 3 min.

ACTIVE INGREDIENT

didecyl dimethyl ammonium chloride

keep out of reach of children

PURPOSE

Disinfection
Sterilization

WARNINGS

1.Only for external use.Not take it ora.
2.Sealed, store the product in a cool and dry place.